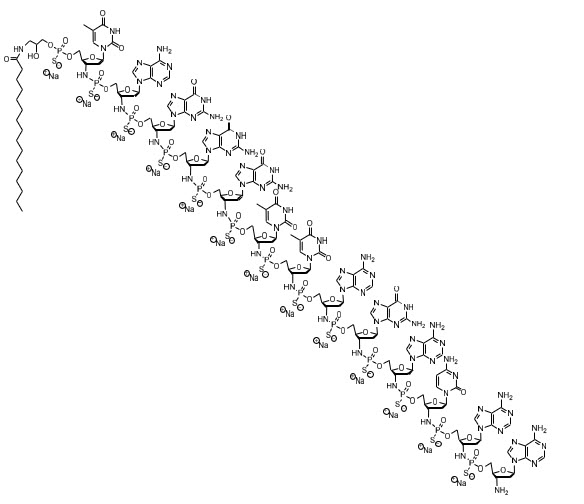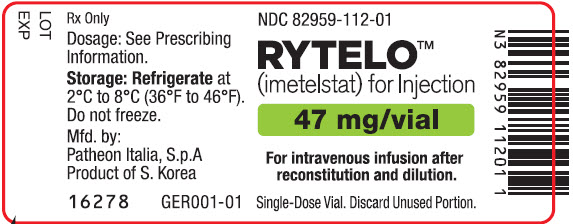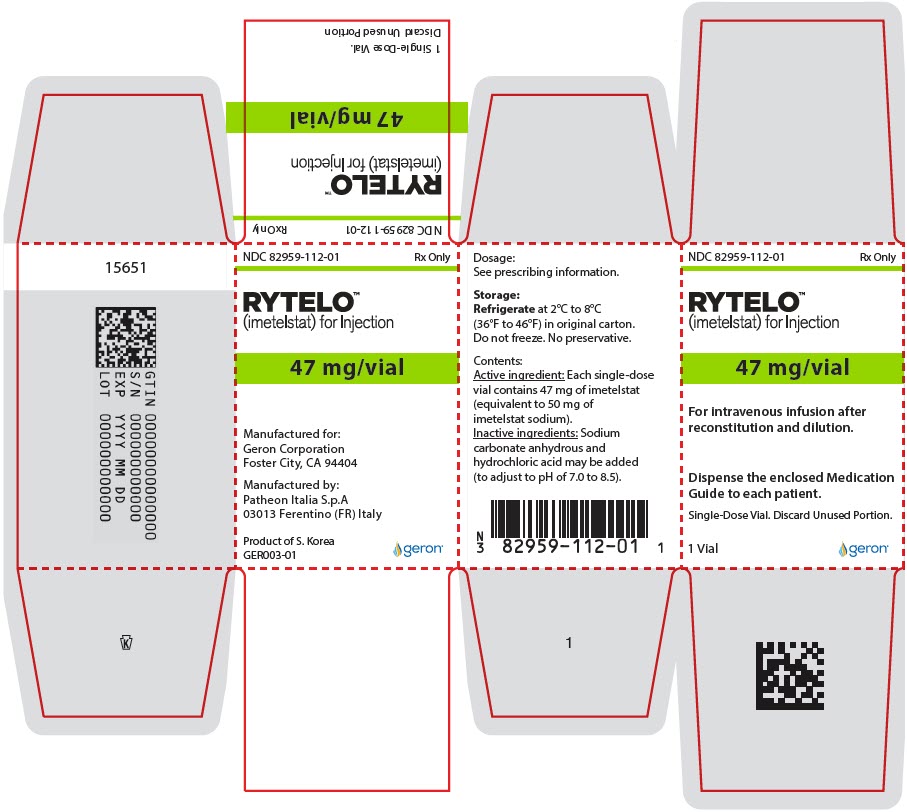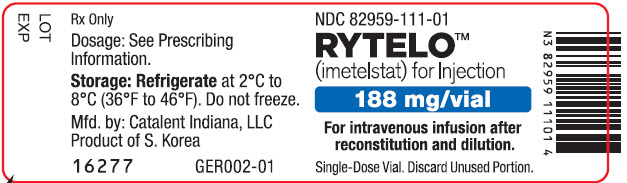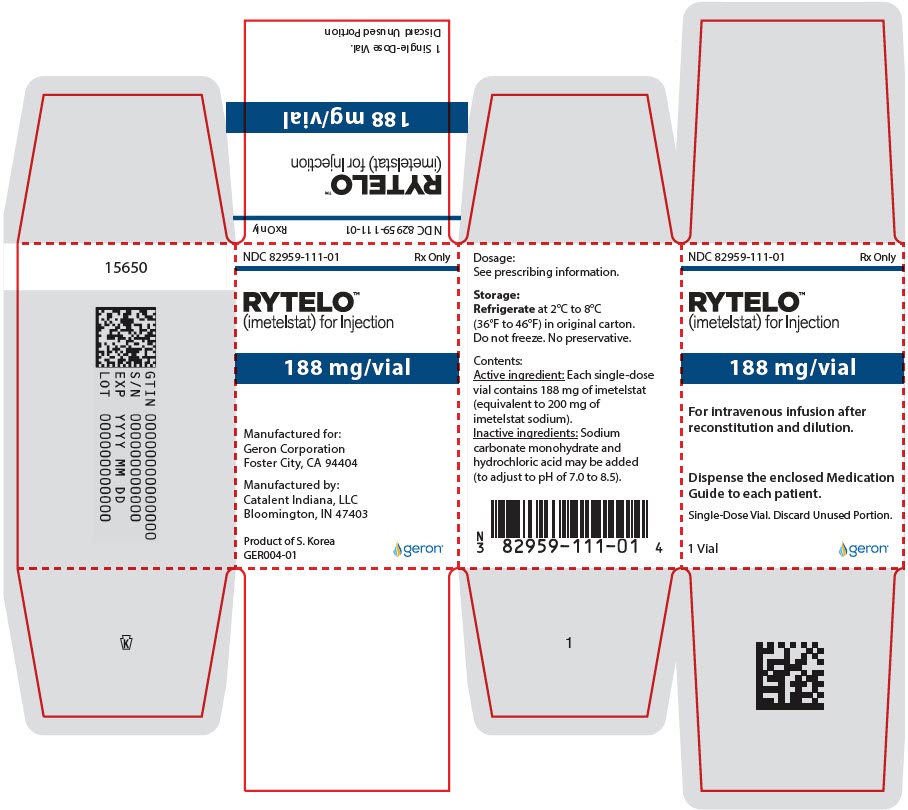 DRUG LABEL: RYTELO
NDC: 82959-112 | Form: INJECTION, POWDER, LYOPHILIZED, FOR SOLUTION
Manufacturer: Geron Corporation
Category: prescription | Type: HUMAN PRESCRIPTION DRUG LABEL
Date: 20251219

ACTIVE INGREDIENTS: imetelstat sodium 47 mg/1 1
INACTIVE INGREDIENTS: sodium carbonate; hydrochloric acid

HIGHLIGHTS OF PRESCRIBING INFORMATION

These highlights do not include all the information needed to use RYTELO safely and effectively. See full prescribing information for RYTELO.
RYTELO (imetelstat) for injection, for intravenous use.
Initial U.S. Approval: 2024

1. INDICATIONS AND USAGE

RYTELO is an oligonucleotide telomerase inhibitor indicated for the treatment of adult patients with low- to intermediate-1 risk myelodysplastic syndromes (MDS) with transfusion-dependent anemia requiring 4 or more red blood cell units over 8 weeks who have not responded to or have lost response to or are ineligible for erythropoiesis-stimulating agents (ESA). (1)

2. DOSAGE AND ADMINISTRATION

- The recommended dosage of RYTELO is 7.1 mg/kg administered as an intravenous infusion over 2 hours every 4 weeks. (2.1)
- Premedicate prior to dosing with RYTELO for potential infusion-related reactions. (2.2)
- See full prescribing information for preparation and administration instructions. (2.4)

3. DOSAGE FORMS AND STRENGTHS

- For injection: 47 mg powder in a single-dose vial for reconstitution. (3)
- For injection: 188 mg powder in a single-dose vial for reconstitution. (3)

4. CONTRAINDICATIONS

None. (4)

5. WARNINGS AND PRECAUTIONS

- Thrombocytopenia: Grade 3 and Grade 4 thrombocytopenia occurred; obtain complete blood cell counts prior to initiation of RYTELO, weekly for the first two cycles, and prior to each cycle thereafter to monitor. Delay or dose reduce as recommended. (2.3, 5.1)
- Neutropenia: Grade 3 and Grade 4 neutropenia occurred; obtain complete blood cell counts prior to initiation of RYTELO, weekly for the first two cycles, and prior to each cycle thereafter to monitor. Delay or dose reduce as recommended. (2.3, 5.2)
- Infusion-Related Reactions: Premedicate before infusion. Interrupt, decrease the rate of infusion, or permanently discontinue RYTELO based on severity. (2.2, 2.3, 5.3)
- Embryo-Fetal Toxicity: Can cause embryo-fetal harm. Advise females of reproductive potential of potential risk to a fetus and to use effective contraception. (5.4, 8.1, 8.3)

6. ADVERSE REACTIONS

Most common adverse reactions (incidence ≥10% with a difference between arms of >5% compared to placebo), including laboratory abnormalities are decreased platelets, decreased white blood cells, decreased neutrophils, increased AST, increased alkaline phosphatase, increased ALT, fatigue, prolonged partial thromboplastin time, arthralgia/myalgia, COVID-19 infections, and headache. (6.1)

To report SUSPECTED ADVERSE REACTIONS, contact Geron Corporation at 1-855-437-6664 (1-855-GERONMI) or FDA at 1-800-FDA-1088 or www.fda.gov/medwatch.

8. USE IN SPECIFIC POPULATIONS

Lactation: Advise not to breastfeed. (8.2)

FULL PRESCRIBING INFORMATION

1. INDICATIONS AND USAGE

RYTELO is indicated for the treatment of adult patients with low- to intermediate-1 risk myelodysplastic syndromes (MDS) with transfusion-dependent anemia requiring 4 or more red blood cell units over 8 weeks who have not responded to or have lost response to or are ineligible for erythropoiesis-stimulating agents (ESA).

2. DOSAGE AND ADMINISTRATION

2.1. Recommended Dosage

The recommended dosage of RYTELO is 7.1 mg/kg administered as an intravenous infusion over 2 hours every 4 weeks. Discontinue RYTELO if a patient does not experience a decrease in red blood cell (RBC) transfusion burden after 24 weeks of treatment (administration of 6 doses) or if unacceptable toxicity occurs at any time [see Dosage and Administration (2.3)].

2.2. Recommended Premedications

Administer the following pre-treatment medications at least 30 minutes prior to dosing to prevent or reduce potential infusion-related reactions:

- diphenhydramine (or equivalent) 25 mg to 50 mg, intravenously or orally
- hydrocortisone (or equivalent) 100 mg to 200 mg, intravenously or orally

Monitor patients for adverse reactions for at least one hour after the infusion has been completed [see Warnings and Precautions (5.3) and Adverse Reactions (6.1)].

2.3. Dosage Modifications for Adverse Reactions

Recommended dose reductions for Grade 3 and Grade 4 adverse reactions are found in Table 1.

The management of Grade 3 and Grade 4 adverse reactions may require temporary dose delay, dose reduction, or treatment discontinuation and are presented in Table 2 and Table 3. RYTELO treatment should be permanently discontinued if the patient cannot tolerate the lowest dose level of 4.4 mg/kg.

Table 1: Recommended Dose Reduction for RYTELO for Grade 3 and Grade 4 Adverse Reactions
Dose Reduction | Dose Every 4 Weeks
First dose reduction | 5.6 mg/kg
Second dose reduction | 4.4 mg/kg

Dosage Modifications for Hematologic (Grade 3 and Grade 4) Adverse Reactions

Monitor complete blood cell counts prior to administration of RYTELO, weekly for the first two cycles, prior to each cycle thereafter, and as clinically indicated. Delay the next cycle if absolute neutrophil count is less than 1 × 10^9/L or platelets are less than 50 × 10^9/L. Modify dose as described in Table 2.

Table 2: Dosage Modifications for Patients with Hematologic Adverse Reactions (Grade 3 and Grade 4)
Adverse Reaction | Severity Grade [Severity based on National Cancer Institute Common Terminology Criteria for Adverse Events Version 4.03.] | Occurrence | Treatment Modification
Thrombocytopenia [see Warnings and Precautions (5.1)] | Grade 3 | First | Delay RYTELO until recovery of platelets to 50 × 10^9/L; restart at same dose level.
Thrombocytopenia [see Warnings and Precautions (5.1)] | Grade 3 | Second and Third | Delay RYTELO until recovery of platelets to 50 × 10^9/L; restart at one dose level lower.
Thrombocytopenia [see Warnings and Precautions (5.1)] | Grade 3 | Fourth | Discontinue RYTELO.
Thrombocytopenia [see Warnings and Precautions (5.1)] | Grade 4 | First and Second | Delay RYTELO until recovery of platelets to 50 × 10^9/L; restart at one dose level lower.
Thrombocytopenia [see Warnings and Precautions (5.1)] | Grade 4 | Third | Discontinue RYTELO.
Neutropenia [see Warnings and Precautions (5.2)] | Grade 3 | First | Delay RYTELO until recovery of ANC to 1 × 10^9/L; restart at same dose level.
 | Grade 3 | Second and Third | Delay RYTELO until recovery of ANC to 1 × 10^9/L; restart at one dose level lower.
 | Grade 3 | Fourth | Discontinue RYTELO.
 | Grade 4 | First and Second | Delay RYTELO until recovery of ANC to 1 × 10^9/L; restart at one dose level lower.
 |  | Third | Discontinue RYTELO.
Abbreviation: ANC = absolute neutrophil count

Dosage Modifications for Non-hematologic Adverse Reactions

Dosage modifications for infusion-related reactions and other adverse drug reactions, including elevated liver function tests (LFTs), are described in Table 3. Monitor liver function tests prior to administration of RYTELO, weekly for the first cycle, prior to each cycle thereafter, and as clinically indicated.

Table 3: Dosage Modifications for Patients with Non-hematologic Adverse Reactions
Adverse Reaction | Severity Grade [Severity based on National Cancer Institute Common Terminology Criteria for Adverse Events Version 4.03.] | Occurrence | Treatment Modification
Infusion-Related Reactions [see Warnings and Precautions (5.3)] | Grade 2 or 3 | First and Second | Interrupt the RYTELO infusion until resolution of the adverse reaction or until the intensity of the reaction decreases to Grade 1; restart infusion at 50% of the infusion rate administered prior to the adverse reaction.
Infusion-Related Reactions [see Warnings and Precautions (5.3)] | Grade 2 or 3 | Third | For Grade 2, stop infusion. May restart at next cycle. For Grade 3, permanently discontinue RYTELO.
Infusion-Related Reactions [see Warnings and Precautions (5.3)] | Grade 4 | First | Stop infusion, administer supportive care as appropriate and permanently discontinue RYTELO.
Other adverse reactions including elevated LFTs [see Adverse Reactions (6.1)] | Grade 3 or 4 | First and Second | Delay RYTELO until recovery of adverse reactions to Grade 1 or baseline; restart at one dose level lower.
 |  | Third | Permanently discontinue RYTELO.
Abbreviation: LFT = liver function test

2.4. Preparation and Administration

RYTELO is provided as a lyophilized powder in a single-dose vial for intravenous infusion only and must be reconstituted and diluted prior to administration.

Use aseptic technique to prepare RYTELO.

RYTELO does not contain a preservative.

Reconstitution:

- Calculate the dose of RYTELO needed based on the patient's body weight (kg).
- Determine the number of RYTELO vials needed to achieve the required dose (total mg) per Table 4. More than one vial may be needed to achieve a full dose.
- Remove the RYTELO vials from the refrigerator and allow the vials to sit for 10 minutes to 15 minutes (not to exceed 30 minutes) to adjust to room temperature 20°C to 25°C (68°F to 77°F) before use.
- Reconstitute each vial of RYTELO with the volume of 0.9% Sodium Chloride Injection provided in Table 4 directly onto the lyophilized powder to obtain a concentration of 31.4 mg/mL of imetelstat.

Table 4: Reconstitution Volumes
Strength [Recommended to use the appropriate combination of vial strengths to most closely match the intended dose based on the patient's weight.] | Volume of 0.9% Sodium Chloride Injection for Reconstitution per Vial | Final Concentration of Reconstituted Solution per Vial | Deliverable Volume per Vial
47 mg | 1.8 mL | 31.4 mg/mL [Each vial contains an overfill to account for loss of liquid during preparation and extraction of the reconstituted solution, resulting in the final concentration.] | 1.5 mL
188 mg | 6.3 mL | 31.4 mg/mL | 6 mL

- Swirl each vial gently to avoid foaming until the powder is fully reconstituted (not to exceed 15 minutes). Do not shake.
- Parenteral drug products should be inspected visually for particulate matter and discoloration prior to administration, whenever solution and container permit. The reconstituted solution in each vial should appear as a clear to slightly hazy solution, essentially free of visible contaminants, particles and/or particulates. Do not use if discoloration or particulate matter is present.
- Use the reconstituted solution immediately to prepare the RYTELO diluted solution in the infusion bag.

Dilution:

- Calculate the required volume of the reconstituted RYTELO solution needed to obtain the appropriate dose according to the patient's body weight.
- Withdraw a volume equal to the required reconstituted RYTELO solution from a 500 mL infusion bag of 0.9% Sodium Chloride Injection and discard it.
- Add the required volume of reconstituted RYTELO solution into the infusion bag so that the total final volume of RYTELO solution in the bag is approximately 500 mL. Discard any unused portion of the reconstituted solution remaining in each vial.
- Gently invert the infusion bag at least 5 times to ensure that the reconstituted RYTELO is well-mixed. Do not shake the infusion bag prior to administration.

Diluted RYTELO Solution Storage:

- If not used immediately, ensure that diluted solution for infusion is used within the total timeframes specified below, according to storage temperature:
  - When stored at room temperature 20°C to 25°C (68°F to 77°F):
    The total time from the reconstitution of RYTELO to completion of the intravenous infusion should not exceed 18 hours from the time of reconstitution.
  - When stored refrigerated 2°C to 8°C (36°F to 46°F):
    The total time from the reconstitution of RYTELO to completion of the intravenous infusion should not exceed 48 hours from the time of reconstitution.

Administration:

- Administer the diluted RYTELO solution by intravenous infusion only over a period of 2 hours.

3. DOSAGE FORMS AND STRENGTHS

- For injection: 47 mg of imetelstat supplied as a white to off-white or slightly yellow lyophilized powder in a single-dose vial for reconstitution.
- For injection: 188 mg of imetelstat supplied as a white to off-white or slightly yellow lyophilized powder in a single-dose vial for reconstitution.

4. CONTRAINDICATIONS

None.

5. WARNINGS AND PRECAUTIONS

5.1. Thrombocytopenia

RYTELO can cause thrombocytopenia based on laboratory values. In the clinical trial, new or worsening Grade 3 or 4 decreased platelets occurred in 65% of patients with MDS treated with RYTELO [see Adverse Reactions (6.1)].

Median time to onset of first occurrence of Grade 3 or 4 decreased platelets was 6 weeks (range: 2 to 88 weeks) and median time to recovery from each occurrence of Grade 3 or 4 decreased platelets to Grade 2 or lower, or last value available, was 1.3 weeks (range: 0.1 to 13 weeks). Grade 3 or 4 decreased platelets occurred throughout treatment with RYTELO, with 48% of patients experiencing Grade 3 or Grade 4 thrombocytopenia during cycles 1-3, 31% during cycles 4-6, 33% during cycles 7-12, and 24% during cycles 13 and beyond. Grade 3 or 4 bleeding was seen in 2.5% of patients, including gastrointestinal bleeding (1.7%) and hematuria (0.8%).

Monitor patients with thrombocytopenia for bleeding.

Monitor complete blood cell counts prior to initiation of RYTELO, weekly for the first two cycles, prior to each cycle thereafter, and as clinically indicated. Administer platelet transfusions as appropriate. Delay the next cycle and resume at the same or reduced dose, or discontinue as recommended [see Dosage and Administration (2.3)].

5.2. Neutropenia

RYTELO can cause neutropenia based on laboratory values. In the clinical trial, new or worsening Grade 3 or 4 decreased neutrophils occurred in 72% of patients with MDS treated with RYTELO [see Adverse Reactions (6.1)].

Median time to onset of first occurrence of Grade 3 or 4 decreased neutrophils was 4.6 weeks (range: 1 to 81 weeks) and median time to recovery from each occurrence of Grade 3 or 4 decreased neutrophils to Grade 2 or lower, or last value available, was 1.9 weeks (range: 0 to 16 weeks). Grade 3 or 4 decreased neutrophils occurred throughout treatment with RYTELO, with 65% of patients experiencing Grade 3 or Grade 4 neutropenia during cycles 1-3, 35% during cycles 4-6, 32% during cycles 7-12, and 39% during cycles 13 and beyond. Febrile neutropenia occurred in 0.8% and sepsis in 4.2%.

Monitor patients with Grade 3 or 4 neutropenia for infections, including sepsis.

Monitor complete blood cell counts prior to initiation of RYTELO, weekly for the first two cycles, prior to each cycle thereafter, and as clinically indicated. Administer growth factors and anti-infective therapies for treatment or prophylaxis as appropriate. Delay the next cycle and resume at the same or reduced dose, or discontinue as recommended [see Dosage and Administration (2.3)].

5.3. Infusion-Related Reactions

RYTELO can cause infusion-related reactions. In the clinical trial, infusion-related reactions occurred in 8% of patients with MDS treated with RYTELO; Grade 3 or 4 infusion-related reactions occurred in 1.7%, including hypertensive crisis (0.8%). The most common infusion-related reaction was headache (4.2%). Infusion-related reactions usually occur during or shortly after the end of the infusion.

Premedicate patients at least 30 minutes prior to infusion with diphenhydramine and hydrocortisone as recommended and monitor patients for at least one hour following the infusion as recommended [see Dosage and Administration (2.2)]. Manage symptoms of infusion-related reactions with supportive care and infusion interruptions, decrease infusion rate, or permanently discontinue as recommended [see Dosage and Administration (2.3)].

5.4. Embryo-Fetal Toxicity

Based on findings in animals, RYTELO can cause embryo-fetal harm when administered to a pregnant woman. In animal reproduction studies, administration of imetelstat to pregnant mice during the period of organogenesis resulted in embryo-fetal mortality at maternal exposures (AUC) 2.5-times the human exposure at the recommended clinical dose. Advise pregnant women of the potential risk to a fetus. Advise females of reproductive potential to use effective contraception during treatment with RYTELO and for 1 week after the last dose [see Use in Specific Populations (8.1, 8.3)].

6. ADVERSE REACTIONS

The following clinically significant adverse reactions are described elsewhere in the labeling:

- Thrombocytopenia [see Warnings and Precautions (5.1)]
- Neutropenia [see Warnings and Precautions (5.2)]
- Infusion-Related Reactions [see Warnings and Precautions (5.3)]

6.1. Clinical Trials Experience

Because clinical trials are conducted under widely varying conditions, adverse reaction rates observed in the clinical trials of a drug cannot be directly compared to rates in the clinical trials of another drug and may not reflect the rates observed in practice.

Low- to Intermediate-Risk Myelodysplastic Syndromes

The safety of RYTELO was evaluated in a randomized, double-blind, placebo-controlled, multicenter trial (IMerge) in 177 adult patients with International Prognostic Scoring System (IPSS) low- to intermediate-1 risk MDS who were transfusion-dependent and relapsed or refractory to or ineligible for ESA treatment [see Clinical Studies (14)]. The safety population included patients who received at least one dose of either RYTELO (n=118) or placebo (n=59) at 7.1 mg/kg as an intravenous infusion administered over two hours every 4 weeks. The median time on treatment with RYTELO was 8 months (range, 0 to 38 months); 69% of patients were exposed to RYTELO for 24 weeks or longer and 45% were exposed for 48 weeks or longer.

The median age of patients who received at least one dose of RYTELO was 72 years (range: 44 to 87 years) with 77% of patients 65 years of age and older and 30% of patients 75 years of age and older. Participants were 60% male, 81% White, 7% Asian, and 0.8% Black.

Serious adverse reactions occurred in 32% of patients who received RYTELO. Serious adverse reactions in > 2% of patients included sepsis (4.2%), fracture (3.4%), cardiac failure (2.5%), and hemorrhage (2.5%). Fatal adverse reactions occurred in 0.8% of patients who received RYTELO, including sepsis (0.8%).

Permanent discontinuation of RYTELO due to an adverse reaction occurred in 15% of patients. Adverse reactions which resulted in permanent discontinuation of RYTELO in > 2% of patients included neutropenia and thrombocytopenia.

Dosage interruptions of RYTELO due to an adverse reaction occurred in 80% of patients. Adverse reactions which required dosage interruption in > 5% of patients included neutropenia, thrombocytopenia and infections.

Dose reductions of RYTELO due to an adverse reaction occurred in 49% of patients. Adverse reactions which required dose reductions in > 2% of patients included neutropenia and thrombocytopenia.

The most common (≥10% with a difference between arms of >5% compared to placebo) adverse reactions, including laboratory abnormalities, were decreased platelets, decreased white blood cells, decreased neutrophils, increased AST, increased alkaline phosphatase, increased ALT, fatigue, prolonged partial thromboplastin time, arthralgia/myalgia, COVID-19 infections, and headache.

Table 5 summarizes the adverse reactions in IMerge.

Table 5: Adverse Reactions (≥5%) in Patients with MDS Who Received RYTELO with a Difference Between Arms of >2% Compared to Placebo in IMerge
Adverse Reaction | RYTELO (N=118) |  | Placebo (N=59)
 | All Grades % | Grades 3 or 4 % | All Grades % | Grades 3 or 4 %
General disorders and administrative site conditions
Fatigue [Fatigue: asthenia, fatigue, and malaise.] | 29 | 0 | 20 | 3.4
Musculoskeletal and connective tissue disorders
Arthralgia/myalgia [Arthralgia/myalgia: arthralgia, back pain, bone pain, musculoskeletal pain, myalgia, neck pain, non-cardiac chest pain, pain, pain in extremity, pain in jaw, and pelvic pain.] | 25 | 2.5 | 19 | 5
Infections and infestations
COVID-19 [COVID-19: asymptomatic COVID-19, COVID-19, COVID-19 pneumonia, and SARS-CoV-2 antibody test positive.] | 19 | 1.7 | 14 | 5
Urinary tract infection [Urinary tract infection: cystitis, Escherichia urinary tract infection, renal abscess, and urinary tract infection.] | 9 | 2.5 | 7 | 0
Nervous system disorders
Headache | 13 | 0.8 | 5 | 0
Syncope [Syncope: fall, pre-syncope, and syncope.] | 7 | 1.7 | 1.7 | 0
Immune system disorders
Infusion-related reactions [Infusion-related reactions: abdominal pain, arthralgia, asthenia, back pain, bone pain, diarrhea, erythema, headache, hypertensive crisis, malaise, non-cardiac chest pain, pruritus, and urticaria. Only events considered related to infusion-related reactions are included.] | 8 | 1.7 | 3.4 | 0
Respiratory, thoracic and mediastinal disorders
Epistaxis | 7 | 0 | 0 | 0
Vascular disorders
Hematoma | 6 | 0 | 0 | 0
Skin and subcutaneous tissue disorders
Pruritus | 6 | 0 | 1.7 | 0
Cardiac disorders
Atrial arrhythmia [Atrial arrhythmia: atrial fibrillation and atrial flutter.] | 6 | 1.7 | 3.4 | 1.7
Injury, poisoning and procedural complications
Fractures [Fractures: femur fracture, hand fracture, hip fracture, humerus fracture, lumbar vertebral fracture, and thoracic vertebral fracture.] | 5 | 3.4 | 1.7 | 1.7
Graded according to National Cancer Institute Common Terminology Criteria for Adverse Events Version 4.03.

Clinically relevant adverse reactions in < 5% of patients who received RYTELO included febrile neutropenia, sepsis, gastrointestinal hemorrhage, and hypertension.

Table 6 summarizes the laboratory abnormalities in IMerge.

Table 6: Select Laboratory Abnormalities (≥10%) That Worsened from Baseline in Patients with MDS Who Received RYTELO with a Difference Between Arms of >2% Compared to Placebo in IMerge
Laboratory Abnormality | RYTELO [The denominator used to calculate the rate varied from 97 to 118 based on the number of patients with a baseline value and at least one post-treatment value.] |  | Placebo [The denominator used to calculate the rate varied from 50 to 59 based on the number of patients with a baseline value and at least one post-treatment value.]
 | All Grades (%) | Grade 3 or 4 (%) | All Grades (%) | Grade 3 or 4 (%)
Hematology
Platelet count decreased | 97 | 65 | 34 | 8
White blood cell count decreased | 94 | 53 | 59 | 1.7
Neutrophil count decreased | 92 | 72 | 47 | 7
PTT prolonged | 26 | 1 | 18 | 4
Chemistry
AST increased | 53 | 0.8 | 22 | 1.7
ALP increased | 48 | 0 | 12 | 0
ALT increased | 43 | 3.4 | 37 | 5
Graded according to National Cancer Institute Common Terminology Criteria for Adverse Events Version 4.03.
ALP = alkaline phosphatase; ALT = alanine aminotransferase; AST = aspartate aminotransferase; PTT = partial thromboplastin time

8. USE IN SPECIFIC POPULATIONS

8.1. Pregnancy

Risk Summary

Based on findings in animal studies, RYTELO can cause embryo-fetal harm when administered to a pregnant woman. There are no available data on RYTELO use in pregnant women to evaluate for drug-associated risk. In embryo-fetal developmental toxicity studies, administration of imetelstat to pregnant mice and rabbits during the period of organogenesis resulted in embryo-fetal mortality, which in mice occurred at maternal exposures approximately 2.5 times the human exposure at the recommended clinical dose. Advise pregnant women of the potential risk to a fetus [see Data].

In the U.S. general population, the estimated background risk of major birth defects and miscarriage in clinically recognized pregnancies is 2% to 4% and 15% to 20%, respectively.

Data

Animal Data

In embryo-fetal developmental toxicity studies, imetelstat was administered by IV bolus injection at doses of 4.7, 9.4, 14.1 or 28.2 mg/kg/day on gestation days 6, 9, and 12 in mice, or by 2-hour intravenous infusion at doses of 4.7, 14.1, or 28.2 mg/kg on gestation days 6 and 13 in rabbits. In rabbits, the dose of 28.2 mg/kg was maternally toxic. Increased post-implantation loss due to an increase in early resorptions, resulting in a decrease in viable fetuses and litter was noted in mice at 28.2 mg/kg and in rabbits starting at 14.1 mg/kg; corresponding to exposures (based on AUC) that are approximately 2.5-times (mice) or 9.3-times (rabbits) the human exposure at the recommended clinical dose.

8.2. Lactation

Risk Summary

There is no data on the presence of imetelstat in human milk, or the effects RYTELO on the breastfed child, or milk production. Because of the potential for adverse reactions in breastfed children, advise women not to breastfeed during treatment with RYTELO and for 1 week after the last dose.

8.3. Females and Males of Reproductive Potential

Based on findings from animal studies, RYTELO can cause embryo-fetal harm when administered to a pregnant woman [see Use in Specific Populations (8.1)].

Pregnancy Testing

Verify the pregnancy status of females of reproductive potential prior to initiating treatment with RYTELO.

Contraception

Females

Advise females of reproductive potential to use effective contraception during treatment with RYTELO and for 1 week after the last dose [see Use in Specific Populations (8.1)].

Infertility

Females

Based on findings in animals, RYTELO may impair fertility in females of reproductive potential. The effect on fertility is reversible [see Nonclinical Toxicology (13.1)].

8.4. Pediatric Use

Safety and effectiveness of RYTELO in pediatric patients have not been established.

8.5. Geriatric Use

Of the 118 patients with low- to intermediate-1 risk myelodysplastic syndromes (MDS) in the clinical trial who received RYTELO, 91 (77.1%) patients were 65 years of age and older and 35 (29.7%) patients 75 years of age and older. No differences in safety or efficacy were observed between older (≥ 65 years) and younger patients.

11. DESCRIPTION

RYTELO for injection contains imetelstat, an oligonucleotide telomerase inhibitor for intravenous use. Imetelstat sodium is a white to off-white or slightly yellow, amorphous, solid powder. It is highly soluble in aqueous solutions, including in 0.9% Sodium Chloride Injection, at both refrigerated and room temperatures. Imetelstat sodium is hygroscopic.

The chemical name for the imetelstat sodium drug substance is DNA, d(3'-amino-3'-deoxy-P-thio) (T-A-G-G-G-T-T-A-G-A-C-A-A), 5'-[O-[2-hydroxy-3-(hexadecanoylamino)propyl] phosphorothioate], sodium salt (1:13). The molecular formula is C148H198N68O53P13S13Na13 (as sodium salt), which equates to a formula weight of 4896 g/mol. The molecular formula for the free acid form is C148H211N68O53P13S13 which equates to a formula weight of 4610 g/mol. The structural formula for imetelstat sodium is:

RYTELO (imetelstat) for injection is a sterile, preservative-free, white to off-white or slightly yellow lyophilized powder for intravenous infusion after reconstitution and dilution. Each single-dose vial provides either 47 mg of imetelstat (equivalent to 50 mg imetelstat sodium) or 188 mg of imetelstat (equivalent to 200 mg imetelstat sodium). The following inactive ingredients may be added during manufacturing: sodium carbonate anhydrous (for the 47 mg preparation) / sodium carbonate monohydrate (for the 188 mg preparation) or hydrochloric acid (to adjust to pH of 7.0 to 8.5).

12. CLINICAL PHARMACOLOGY

12.1. Mechanism of Action

Imetelstat is an oligonucleotide human telomerase inhibitor that binds to the template region of the RNA component of human telomerase (hTR), inhibits telomerase enzymatic activity and prevents telomere binding.

Increased telomerase activity and human telomerase reverse transcriptase (hTERT) RNA expression have been reported in MDS and malignant stem and progenitor cells. Nonclinical studies showed imetelstat treatment led to reduction of telomere length, reduction of malignant stem and progenitor cell proliferation, and induction of apoptotic cell death.

12.2. Pharmacodynamics

Grade 3 and 4 Thrombocytopenia

Higher imetelstat exposure is associated with higher incidence of Grade 3 and 4 thrombocytopenia in patients with MDS.

12.3. Pharmacokinetics

Imetelstat plasma geometric mean (coefficient of variation [CV] %) maximum concentration (Cmax) is 18.3 µM (27.3%) and the area under the concentration-time curve from time 0 to 28 days (AUC0-28) was 114.2 h*µM (43.2%). Imetelstat does not accumulate between treatment cycles.

Distribution

Following a single intravenous dose of 7.1 mg/kg of RYTELO administered over 2 hours in patients with MDS, the geometric mean (CV%) volume of distribution is approximately 14.1 L (27.2%). In vitro human plasma protein binding is greater than 94%.

Elimination

The imetelstat geometric mean (CV%) apparent plasma half-life is approximately 4.9 hours (43.2%) at the approved recommended dosage.

Metabolism

Imetelstat is expected to be metabolized by nucleases to nucleotides of various lengths.

Specific populations

No clinically significant differences in the pharmacokinetics of imetelstat were observed based on age (21 to 87 years), sex, race (81% White, 4% Asian, 7% Black, 8% other/unknown), mild to moderate renal impairment (CLcr 30 to < 90 mL/min), mild hepatic impairment (total bilirubin ≤ ULN and AST > ULN, or total bilirubin > 1× to 1.5× ULN and any AST), or moderate hepatic impairment (total bilirubin > 1.5× to 3× ULN and any AST). The effect of severe renal impairment (CLcr 15 to < 30 mL/min), end-stage renal disease, or severe hepatic impairment (total bilirubin > 3× ULN and any AST) has not been established.

Drug Interaction Studies

In Vitro Studies

CYP Enzymes: Imetelstat is not an inhibitor or inducer of CYP450 enzymes.

Transporter systems: Imetelstat is an inhibitor of OATP1B1 and OATP1B3.

12.6. Immunogenicity

The observed incidence of anti-drug antibodies (ADA) is highly dependent on the sensitivity and specificity of the assay. Differences in assay methods preclude meaningful comparisons of the incidence of anti-drug antibodies in the studies described below with the incidence of anti-drug antibodies in other studies, including those of RYTELO.

Seventeen percent (28/166) of evaluable patients with low- or intermediate-1 risk MDS tested positive for imetelstat anti-drug antibodies, with a median onset of 38 weeks following the study drug dosage of RYTELO for a median duration of treatment of 35 weeks in Phase 2 and Phase 3 of the IMerge study. There was no clinically significant effect of ADA on the PK, safety, or efficacy of RYTELO among the study participants who developed anti-drug antibodies.

13. NONCLINICAL TOXICOLOGY

13.1. Carcinogenesis, Mutagenesis, Impairment of Fertility

Carcinogenicity studies have not been conducted with imetelstat.

In vitro, imetelstat was not mutagenic in the bacterial mutagenicity assay (Ames test) or clastogenic in the chromosomal aberrations assay using cultured human peripheral blood lymphocytes. Imetelstat was not genotoxic in an in vivo mouse micronucleus assay at intravenous dose levels up to approximately 104 mg/kg.

Fertility studies have not been conducted with imetelstat. Female monkeys given 14.1 mg/kg once weekly for 9 months exhibited uterine endometrial atrophy in a general toxicology study. This effect was observed at a mean exposure (based on AUC) that is approximately 14.4-times the human exposure at the recommended clinical dose. This finding was not present in animals following a 14-week recovery period.

14. CLINICAL STUDIES

14.1. Myelodysplastic Syndromes (MDS)

The efficacy of RYTELO was evaluated in a randomized, double-blind, placebo-controlled, multicenter trial (IMerge; NCT02598661) in 178 patients enrolled with International Prognostic Scoring System (IPSS) low- or intermediate-1 risk MDS who were transfusion-dependent (requiring ≥ 4 red blood cell (RBC) units over an 8-week period during the 16 weeks prior to randomization). Eligible patients were required to have failed to respond or have lost response or be ineligible for erythropoiesis-stimulating agents (ESAs); and had an absolute neutrophil count of 1.5 × 10^9/L or greater and platelets 75 × 10^9/L or greater. Patients were ineligible if they had del(5q) cytogenetic abnormality or had received prior treatment with lenalidomide or hypomethylating agents.

Participants were randomized in a 2:1 ratio to receive an intravenous infusion of RYTELO (n=118) 7.1 mg/kg or placebo (n=60) in 28-day treatment cycles until disease progression, unacceptable toxicity, or withdrawal from the study. Randomization was stratified by prior RBC transfusion burden and by IPSS risk group. All patients received supportive care, which included RBC transfusions.

Of the 178 patients enrolled, the median age was 72 years (range: 39 to 87 years), with 62% male, and 80% White, 6% Asian, 1.7% Black, 12% other or not reported. The key baseline disease characteristics of the efficacy population are shown in Table 7.

Table 7: Baseline Disease Characteristics of Patients with MDS in IMerge
Disease Characteristic | RYTELO (N=118) | Placebo (N=60)
Time since original diagnosis
Median years (range) | 3.5 (0.1, 26.7) | 2.8 (0.2, 25.7)
ECOG Score (0, 1, 2), n (%)
0: Asymptomatic | 42 (35.6) | 21 (35)
1: Symptomatic fully ambulatory | 70 (59.3) | 39 (65)
2: Symptomatic in bed less than 50% of the day | 6 (5.1) | 0
IPSS Risk Classification, n (%)
Low | 80 (67.8) | 39 (65)
Intermediate-1 | 38 (32.2) | 21 (35)
Prior RBC transfusion burden [Prior RBC transfusion burden is defined as the maximum number of RBC units transfused over an 8-week period during the 16 weeks prior to randomization.] , n (%)
4 to 6 units | 62 (52.5) | 33 (55)
> 6 units | 56 (47.5) | 27 (45)
WHO Classification (2008), n (%)
RS+ [RS+ includes refractory anemia with ring sideroblasts (RARS)/refractory cytopenia with multilineage dysplasia and ≥ 15% ringed sideroblasts (RCMD-RS).] | 73 (61.9) | 37 (61.7)
RS˗ [RS˗ includes others.] | 44 (37.3) | 23 (38.3)
Missing | 1 (0.8) | 0
Baseline sEPO, n (%)
≤ 500 mU/mL | 87 (73.7) | 36 (60)
> 500 mU/mL | 26 (22) | 22 (36.7)
Missing | 5 (4.2) | 2 (3.3)
Prior ESA Use, n (%)
Yes | 108 (91.5) | 52 (86.7)
No | 10 (8.5) | 8 (13.3)
Baseline blood counts, median
Neutrophils (cells/L) | 2.6 × 10^9 | 2.7 × 10^9
Hemoglobin (g/dL) | 7.9 | 7.8
Platelets (cells/L) | 230 × 10^9 | 230 × 10^9
Abbreviations: ECOG = Eastern Cooperative Oncology Group; ESA = erythropoietin stimulating agents; IPSS = International Prognostic Scoring System; RBC = Red Blood Cell; MDS = myelodysplastic syndromes; sEPO = serum erythropoietin; WHO = World Health Organization

Efficacy was established after a median follow up time of 19.5 months (range: 1.4 to 36.2) in the imetelstat group and 17.5 months (range: 0.7 to 34.3) in the placebo group based upon the proportion of patients who achieved ≥ 8-week and ≥ 24-week RBC-TI, defined as the absence of RBC transfusion(s) during any consecutive 8 weeks (56 days) period, and during any consecutive 24 weeks (168 days) period, respectively, from randomization until the start of subsequent anti-cancer therapy (if any). The efficacy results are summarized in Table 8.

Table 8: Efficacy Results of RYTELO in IMerge
 | RYTELO (N=118) | Placebo (N=60) | % Difference (95% CI) [95% CI based on Wilson Score method.] | p-value [p-value is based on Cochran-Mantel-Haenszel (CMH) controlling for prior RBC transfusion burden (≤ 6 versus >6 units RBC) and IPSS risk group (low versus intermediate-1) applied to randomization.]
Rate of ≥ 8-week RBC TI
≥ 8-week RBC TI, n (%) | 47 (39.8) | 9 (15.0) | 24.8 (9.9, 36.9) | < 0.001
95% CI for response rate (%) [Exact Clopper-Pearson confidence interval.] | (30.9, 49.3) | (7.1, 26.6) | 24.8 (9.9, 36.9) | < 0.001
Rate of ≥ 24-week RBC TI
≥ 24-week RBC TI, n (%) | 33 (28.0) | 2 (3.3) | 24.6
95% CI for response rate (%) | (20.1, 37.0) | (0.4, 11.5) | (12.6, 34.2) | < 0.001
Abbreviations: CI = Confidence Interval; RBC = Red Blood Cell; TI = Transfusion Independence

16. HOW SUPPLIED/STORAGE AND HANDLING

How Supplied

RYTELO (imetelstat) for injection is a preservative free, white to off-white or slightly yellow, lyophilized powder available as:

Carton Contents | NDC
One RYTELO 47 mg single-dose vial | 82959-112-01
One RYTELO 188 mg single-dose vial | 82959-111-01

Storage

Store vials refrigerated at 2°C to 8°C (36°F to 46°F) in original carton.

Do not freeze.

17. PATIENT COUNSELING INFORMATION

Advise the patient to read the FDA-approved patient labeling (Medication Guide).

Discuss the following with patients prior to and during treatment with RYTELO.

Thrombocytopenia

Advise patients of the risk of thrombocytopenia with RYTELO, and that their blood counts will be monitored routinely while on treatment and dose of RYTELO delayed or reduced as needed. Instruct patients to notify a healthcare provider immediately if they show signs or symptoms of thrombocytopenia such as unusual bleeding or bruising [see Warnings and Precautions (5.1)].

Neutropenia

Advise patients of the risk of neutropenia with RYTELO and that their blood counts will be monitored routinely while on treatment and the dose of RYTELO may be delayed or reduced as needed. Instruct patients to notify a healthcare provider immediately if they show signs or symptoms of neutropenia, such as fever or infection [see Warnings and Precautions (5.2)].

Infusion-Related Reactions

Inform patients that infusion-related reactions can occur during treatment with RYTELO and premedications will be given prior to each infusion. Patients will be monitored by their healthcare provider for at least an hour after the infusion [see Dosage and Administration (2.2) and Warnings and Precautions (5.3)].

Advise patients that their healthcare provider may decide to give RYTELO more slowly or stop the infusion if an infusion-related reaction occurs [see Adverse Reactions (6.1)]

Embryo-Fetal Toxicity

Advise pregnant women and females of reproductive potential of the potential risk to a fetus. Advise females of reproductive potential to inform their healthcare provider if they are pregnant or become pregnant [see Warnings and Precautions (5.4) and Use in Specific Populations (8.1)]. Advise females of reproductive potential to use effective contraception during treatment with RYTELO and for 1 week after the last dose [see Use in Specific Populations (8.3)].

Lactation

Advise women not to breastfeed during treatment with RYTELO and for 1 week after the last dose [see Use in Specific Populations (8.2)].

Manufactured for:
Geron Corporation
919 E. Hillsdale Blvd., Suite 250
Foster City, CA 94404

Manufactured by (188 mg vials):
Catalent Indiana, LLC
1300 S Patterson Drive
Bloomington, IN 47403

Manufactured by (47 mg vials):
Patheon Italia, S.p.A
2° Trav. SX Via Morolense, 5
03013 Ferentino (FR), Italy

GER005-01

MEDICATION GUIDE
RYTELO™ (ri-TEL-o)
(imetelstat)
for injection, for intravenous use

What is the most important information I should know about RYTELO?
RYTELO may cause serious side effects, including:

- Low platelet counts (thrombocytopenia). Low platelet counts are common during treatment with RYTELO and can also be severe. Low platelet counts can increase your risk for bleeding. Your healthcare provider may give you platelet transfusions to reduce the risk of bleeding if you develop a low platelet count during treatment with RYTELO. Tell your healthcare provider right away if you develop any signs or symptoms of bleeding, including:

- unusual bleeding or bruising
- bleeding that lasts a long time
- nosebleeds

- vomiting blood
- blood in your stool or black tarry stool

- Low neutrophil counts (neutropenia). Low counts of a type of white blood cell called neutrophils are common during treatment with RYTELO and can also be severe. Low neutrophil counts can increase your risk for infections, including serious infections and sepsis. Your healthcare provider may give you medicines before you start treatment to help prevent neutropenia and infections and may treat you with medicines if you develop these problems during treatment with RYTELO. Tell your healthcare provider right away if you develop any signs or symptoms of infection during treatment with RYTELO, including:

- fever
- shortness of breath or trouble breathing
- cough

- chills
- pain or burning when you urinate

Your healthcare provider will do blood tests to check your platelet and neutrophil counts before starting treatment with RYTELO, weekly for the first 2 cycles of treatment, before you receive each additional cycle, and as needed during your treatment.
Your healthcare provider may delay your next treatment, decrease your dose, or stop treatment with RYTELO if you develop thrombocytopenia or neutropenia during treatment.
See "What are the possible side effects of RYTELO?" for more information about side effects.

What is RYTELO?
RYTELO is a prescription medicine used to treat a condition called low- to intermediate-1 risk myelodysplastic syndromes (MDS) in adults:

- with anemia (low red blood cell counts) who need blood transfusions of 4 or more red blood cell units over 8 weeks and
- who have not responded to, have stopped responding to, or cannot be treated with other medicines called erythropoiesis-stimulating agents (ESAs).

It is not known if RYTELO is safe and effective in children.

Before receiving RYTELO, tell your healthcare provider about all of your medical conditions, including if you:

- are pregnant or plan to become pregnant. RYTELO may harm your unborn baby and may cause loss of pregnancy (miscarriage). Tell your healthcare provider right away if you become pregnant or think you may be pregnant during treatment with RYTELO.
  Females who are able to become pregnant:
  - Your healthcare provider will perform a pregnancy test before you are given RYTELO.
  - You should use effective birth control (contraception) during treatment with RYTELO and for 1 week after your last dose.
- are breastfeeding or plan to breastfeed. It is not known if RYTELO passes into your breastmilk. Do not breastfeed during treatment with RYTELO and for 1 week after your last dose.

Tell your healthcare provider about all the medicines you take, including prescription and over-the-counter medicines, vitamins, and herbal supplements. Know the medicines you take. Keep a list of them to show your healthcare provider and pharmacist when you get a new medicine.

How will I receive RYTELO?

- RYTELO will be given as an intravenous infusion into your vein over a period of 2 hours by your healthcare provider.
- RYTELO is usually given every 4 weeks.
- Your healthcare provider will prescribe RYTELO in a dose that is right for you and may change your dose, change your dosing schedule, or stop treatment depending on how you respond to RYTELO.
- Your healthcare provider will do certain blood tests during treatment with RYTELO to check for side effects and to see how well you respond to treatment.
- Your healthcare provider will decide how long you will continue treatment with RYTELO.

What are the possible side effects of RYTELO?
RYTELO may cause serious side effects, including:

- See "What is the most important information I should know about RYTELO?"
- Infusion-related reactions. RYTELO can cause infusion-related reactions during or after your infusion that can be severe, including a severe sudden increase in blood pressure called hypertensive crisis. Your healthcare provider will give you medicines before each RYTELO infusion to help prevent or lessen infusion-related reactions and will watch you for at least 1 hour after your infusion. If you develop infusion-related reactions, your healthcare provider may infuse RYTELO more slowly, temporarily stop, or permanently stop your treatment. Tell your healthcare provider if you develop any signs or symptoms of infusion-related reactions, including:

- stomach pain
- joint pain
- weakness and tiredness
- back and bone pain
- diarrhea
- redness

- headache
- high blood pressure
- not feeling well
- chest pain that is not related to your heart
- itching
- hives

The most common side effects of RYTELO include:

- decreased platelet counts
- decreased white blood cell counts
- decreased neutrophil counts
- increased liver enzymes (AST, alkaline phosphatase, and ALT)

- tiredness
- longer than usual blood clotting times
- joint, bone and muscle pain
- Covid-19 infections
- headache

RYTELO may cause fertility problems in females. This could affect your ability to get pregnant. Talk to your healthcare provider if this is a concern for you.
These are not all of the possible side effects of RYTELO. Call your doctor for medical advice about side effects. You may report side effects to FDA at 1-800-FDA-1088.

General information about the safe and effective use of RYTELO.
Medicines are sometimes prescribed for purposes other than those listed in a Medication Guide. You can ask your pharmacist or healthcare provider for information about RYTELO that is written for health professionals.

What are the ingredients in RYTELO?
Active ingredient: imetelstat
Inactive ingredients:

- 47 mg: sodium carbonate anhydrous or hydrochloric acid may be added during manufacturing to adjust the pH
- 188 mg: sodium carbonate monohydrate or hydrochloric acid may be added during manufacturing to adjust the pH

Manufactured for: Geron Corporation, 919 E. Hillsdale Blvd., Suite 250, Foster City, CA 94404
Manufactured by (47 mg vials):
Patheon Italia, S.p.A, 2° Trav. SX Via Morolense, 5, 03013 Ferentino (FR), Italy
Manufactured by (188 mg vials):
Catalent Indiana, LLC, 1300 S Patterson Drive, Bloomington, IN 47403
GER006-01
For more information about RYTELO, go to www.RYTELO.com or call 1-866-471-0921.

This Medication Guide has been approved by the U.S. Food and Drug Administration.

Issued: 6/2024

PRINCIPAL DISPLAY PANEL - 47 mg Vial Label

NDC 82959-112-01

RYTELO™
(imetelstat) for Injection

47 mg/vial

For intravenous infusion after
reconstitution and dilution.

Single-Dose Vial. Discard Unused Portion.

PRINCIPAL DISPLAY PANEL - 47 mg Vial Carton

NDC 82959-112-01
Rx Only

RYTELO™
(imetelstat) for Injection

47 mg/vial

For intravenous infusion after
reconstitution and dilution.

Dispense the enclosed Medication
Guide to each patient.

Single-Dose Vial. Discard Unused Portion.

1 Vial
geron®

PRINCIPAL DISPLAY PANEL - 188 mg Vial Label

NDC 82959-111-01

RYTELO™
(imetelstat) for Injection

188 mg/vial

For intravenous infusion after
reconstitution and dilution.

Single-Dose Vial. Discard Unused Portion.

PRINCIPAL DISPLAY PANEL - 188 mg Vial Carton

NDC 82959-111-01
Rx Only

RYTELO™
(imetelstat) for Injection

188 mg/vial

For intravenous infusion after
reconstitution and dilution.

Dispense the enclosed Medication
Guide to each patient.

Single-Dose Vial. Discard Unused Portion.

1 Vial
geron®